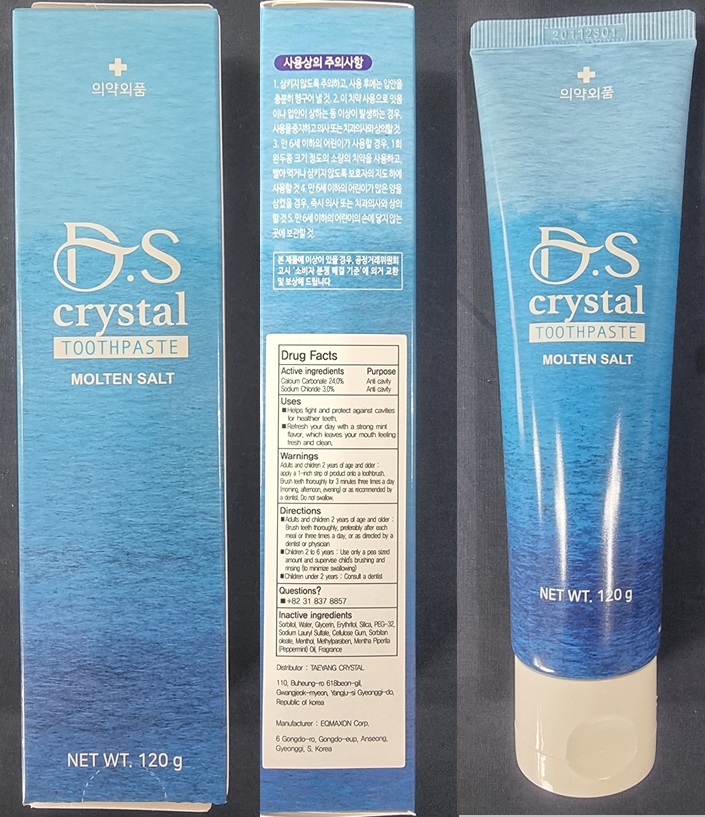 DRUG LABEL: D.S Crystal Tooth
NDC: 81569-010 | Form: PASTE, DENTIFRICE
Manufacturer: Taeyang Crystal
Category: otc | Type: HUMAN OTC DRUG LABEL
Date: 20210223

ACTIVE INGREDIENTS: Calcium Carbonate 28.8 g/120 g; Sodium Chloride 3.6 g/120 g
INACTIVE INGREDIENTS: Sorbitol; Water; Glycerin

ACTIVE INGREDIENTS

Calcium Carbonate 24.0%
Sodium Chloride 3.0%

INACTIVE INGREDIENTS

Sorbitol, Water, Glycerin, Erythritol, Silica, PEG-32, Sodium Lauryl Sulfate, Cellulose Gum, Sorbitan oleate, Menthol, Methylparaben, Mentha Piperita (Peppermint) Oil, Fragrance

PURPOSE

Anti cavity

WARNINGS

Adults and children 2 years of age and older: apply a 1-inch strip of product onto a toothbrush. Brush teeth thoroughly for 3 minutes three times a day (morning, afternoon, evening) or as recommended by a dentist. Do not swallow.

KEEP OUT OF REACH OF CHILDREN

Uses

■ Helps fight and protect against cavities for healthier teeth.
■ Refresh your day with a strong mint flavor, which leaves your mouth feeling fresh and clean.

Directions

■ Adults and children 2 years of age and older: Brush teeth thoroughly, preferably after each meal or three times a day, or as directed by a dentist or physician
■ Children 2 to 6 years: Use only a pea sized amount and supervise child's brushing and rinsing (to minimize swallowing)
■ Children under 2 years: Consult a dentist

QUESTIONS

■ +82-31-837-8857